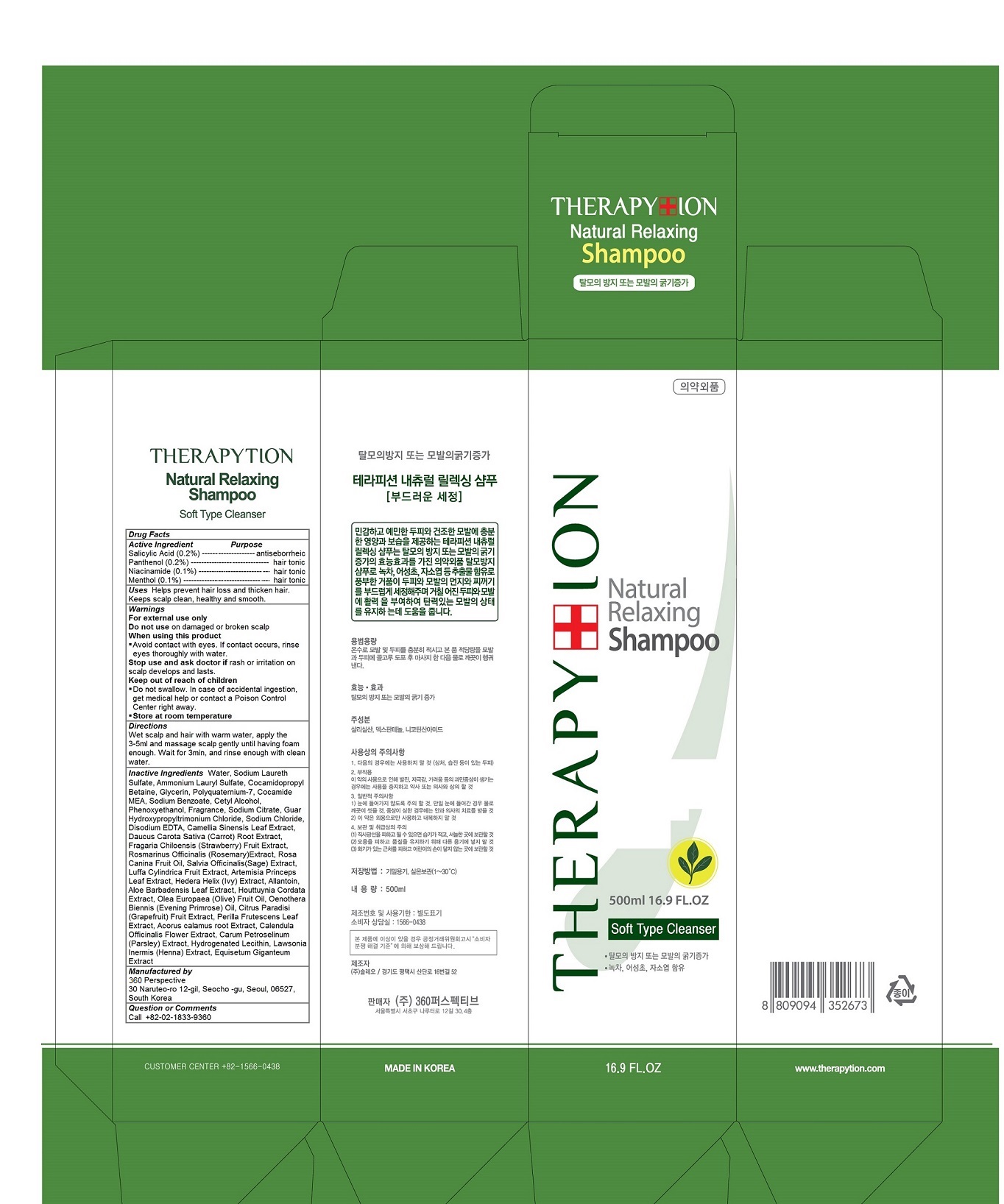 DRUG LABEL: Therapytion Natural Relaxing
NDC: 70477-103 | Form: SHAMPOO
Manufacturer: 360 Perspective
Category: otc | Type: HUMAN OTC DRUG LABEL
Date: 20160419

ACTIVE INGREDIENTS: Panthenol 0.002 1/500 mL; SALICYLIC ACID 0.002 1/500 mL; Niacinamide 0.001 1/500 mL; Menthol 0.001 1/500 mL
INACTIVE INGREDIENTS: WATER; Sodium Laureth Sulfate; Ammonium Lauryl Sulfate; Cocamidopropyl Betaine; Glycerin; POLYQUATERNIUM-7 (70/30 ACRYLAMIDE/DADMAC; 1600000 MW); COCO MONOETHANOLAMIDE; SODIUM BENZOATE; CETYL ALCOHOL; PHENOXYETHANOL; Sodium Citrate; GUAR HYDROXYPROPYLTRIMONIUM CHLORIDE (1.7 SUBSTITUENTS PER SACCHARIDE); SODIUM CHLORIDE; EDETATE DISODIUM; GREEN TEA LEAF; CARROT; BEACH STRAWBERRY; ROSEMARY; ROSA CANINA FRUIT OIL; SALVIA OFFICINALIS ROOT; LUFFA AEGYPTIACA FRUIT; ARTEMISIA PRINCEPS LEAF; HEDERA HELIX LEAF; Allantoin; ALOE VERA LEAF; HOUTTUYNIA CORDATA FLOWERING TOP; OLIVE OIL; EVENING PRIMROSE OIL; GRAPEFRUIT; PERILLA FRUTESCENS TOP; ACORUS CALAMUS ROOT; CALENDULA OFFICINALIS FLOWER; PETROSELINUM CRISPUM

Therapytion Natural Relaxing Shampoo